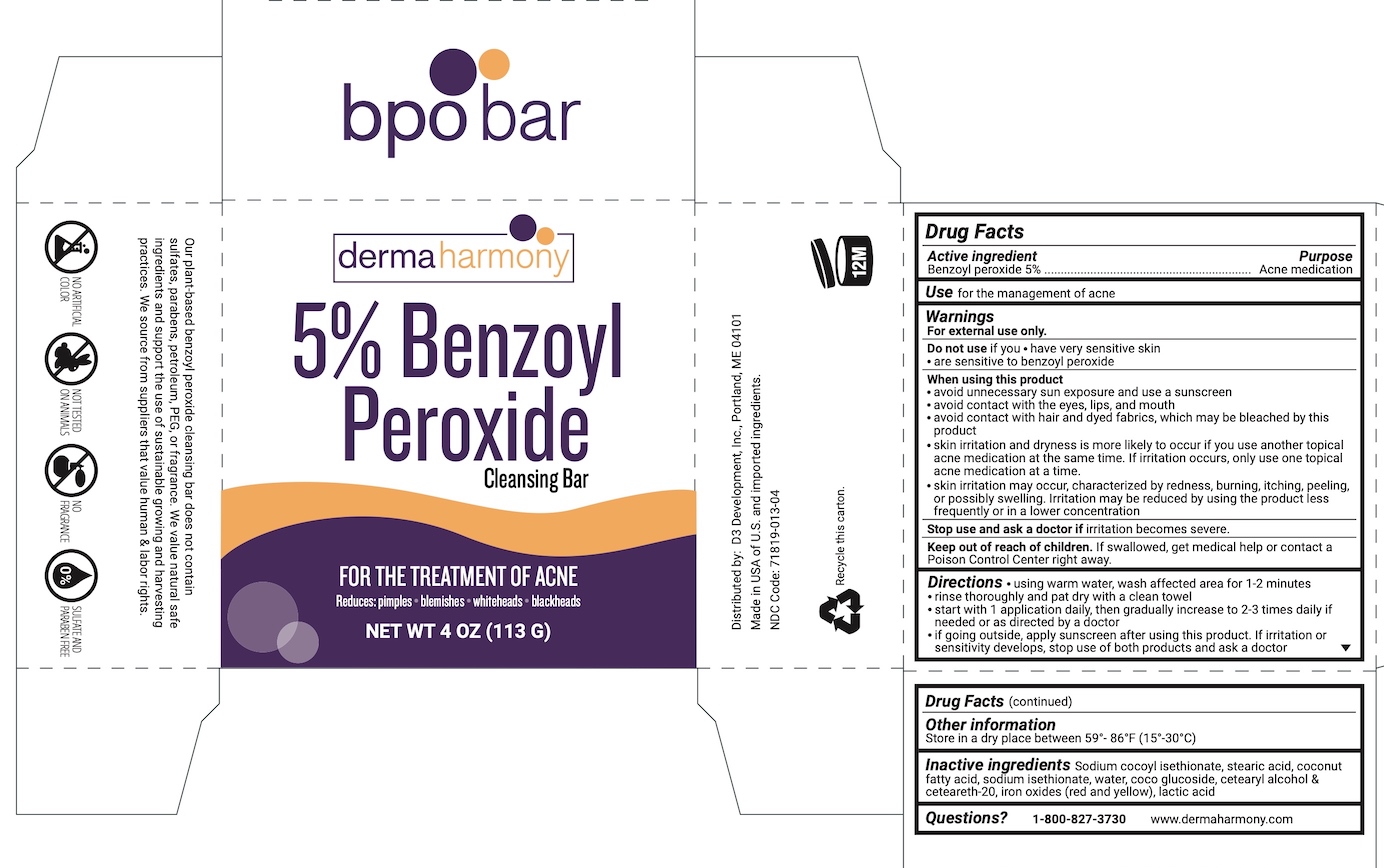 DRUG LABEL: Dermaharmony 5% Benzoyl Peroxide
NDC: 71819-013 | Form: SOAP
Manufacturer: D3 Development, Inc.
Category: otc | Type: HUMAN OTC DRUG LABEL
Date: 20241220

ACTIVE INGREDIENTS: BENZOYL PEROXIDE 5 g/100 g
INACTIVE INGREDIENTS: FERRIC OXIDE YELLOW; FERRIC OXIDE RED; POLYOXYL 20 CETOSTEARYL ETHER; LACTIC ACID; COCO GLUCOSIDE; SODIUM COCOYL ISETHIONATE; STEARIC ACID; COCONUT ACID; CETOSTEARYL ALCOHOL; SODIUM ISETHIONATE; WATER

Dermaharmony 5% Benzoyl Peroxide Bar

Drug Facts

Active ingredient

Benzoyl peroxide 5%

Purpose

Acne medication

Use

for the management of acne

Warnings

For external use only

Do not useif you

- have very sensitive skin
- are sensitive to benzoyl peroxide

When using this product

- avoid unnecessary sun exposure and use a sunscreen
- avoid contact with eyes, lips and mouth
- avoid contact with hair and dyed fabrics, which may be bleached by this product
- skin irritation and dryness is more likely to occur if you use another topical acne medication at the same time. If irritation occurs, only use one topical acne medication at a time.
- skin irritation may occur, characterized by redness, burning, itching, peeling, or possibly swelling. Irritation may be reduced by using the product less frequently or in a lower concentration.

Stop use and ask a doctor ifirritation becomes severe.

Keep out of reach of children.If swallowed, get medical help or contact a Poison Control Center right away.

Directions

- using warm water, wash affected area for 1-2 minutes
- rinse thoroughly and pat dry with a clean towel
- start with 1 application daily, then gradually increase to 2-3 times daily if needed or as directed by a doctor
- if going outside, apply sunscreen after using this product. If irritation or sensitivity develops, stop use of both products and ask a doctor

Other information

Store in a dry place between 59-86°F (15-30°C)

Inactive ingredients

Sodium cocoyl isethionate, stearic acid, coconut fatty acid, sodium isethionate, water. coco glucoside, cetearyl alcohol & ceteareth-20, iron oxides (red and yellow), lactic acid

Questions?

1-800-827-3730

www.dermaharmony.com

Distributed by:

D3 Development, Inc., Portland, ME 04101

Made in USA of U.S. and imported ingredients.

NDC Code: 71819-013-04

PACKAGE LABEL

dermaharmony

5% Benzoyl Peroxide

Cleansing Bar

FOR THE TREATMENT OF ACNE

Reduces: pimples-blemishes-whiteheads-blackheads

NET WT 4 OZ (113G)